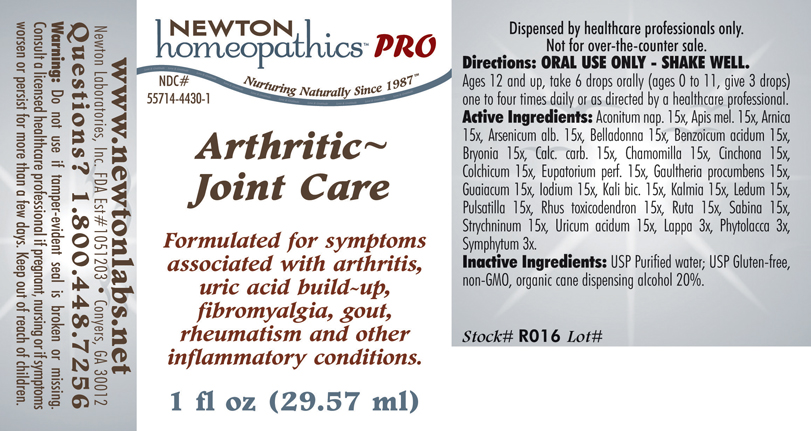 DRUG LABEL: Arthritic Joint Care 
NDC: 55714-4430 | Form: LIQUID
Manufacturer: Newton Laboratories, Inc.
Category: homeopathic | Type: HUMAN PRESCRIPTION DRUG LABEL
Date: 20110601

ACTIVE INGREDIENTS: Aconitum Napellus 15 [hp_X]/1 mL; Apis Mellifera 15 [hp_X]/1 mL; Arnica Montana 15 [hp_X]/1 mL; Arsenic Trioxide 15 [hp_X]/1 mL; Atropa Belladonna 15 [hp_X]/1 mL; Benzoic Acid 15 [hp_X]/1 mL; Bryonia Alba Root 15 [hp_X]/1 mL; Oyster Shell Calcium Carbonate, Crude 15 [hp_X]/1 mL; Matricaria Recutita 15 [hp_X]/1 mL; Cinchona Officinalis Bark 15 [hp_X]/1 mL; Colchicum Autumnale Bulb 15 [hp_X]/1 mL; Eupatorium Perfoliatum Flowering Top 15 [hp_X]/1 mL; Gaultheria Procumbens Top 15 [hp_X]/1 mL; Guaiac 15 [hp_X]/1 mL; Iodine 15 [hp_X]/1 mL; Potassium Dichromate 15 [hp_X]/1 mL; Kalmia Latifolia Leaf 15 [hp_X]/1 mL; Ledum Palustre Twig 15 [hp_X]/1 mL; Pulsatilla Vulgaris 15 [hp_X]/1 mL; Toxicodendron Pubescens Leaf 15 [hp_X]/1 mL; Ruta Graveolens Flowering Top 15 [hp_X]/1 mL; Juniperus Sabina Leafy Twig 15 [hp_X]/1 mL; Strychnine 15 [hp_X]/1 mL; Uric Acid 15 [hp_X]/1 mL; Arctium Lappa Root 3 [hp_X]/1 mL; Phytolacca Americana Root 3 [hp_X]/1 mL; Comfrey Root 3 [hp_X]/1 mL

Arthritic~Joint Care

PRODUCT NAME & INDICATIONS SECTION

Arthritic~Joint Care Formulated for symptoms associated with arthritis, uric acid build-up, fibromyalgia, gout, rheumatism and other inflammatory conditions.

DIRECTION SECTION

Directions: ORAL USE ONLY - SHAKE WELL. Ages 12 and up, take 6 drops orally (ages 0 to 11, give 3 drops) one to four times daily or as directed by a healthcare professional.

ACTIVE INGREDIENT SECTION

Aconitum nap. 15x, Apis mel. 15x, Arnica15x, Arsenicum alb. 15x, Belladonna 15x, Benzoicum acidum 15x,Bryonia 15x, Calc. carb. 15x, Chamomilla 15x, Cinchona 15x,Colchicum 15x, Eupatorium perf. 15x, Gaultheria procumbens 15x,Guaiacum 15x, Iodium 15x, Kali bic. 15x, Kalmia 15x, Ledum 15x,Pulsatilla 15x, Rhus toxicodendron 15x, Ruta 15x, Sabina 15x,Strychninum 15x, Uricum acidum 15x, Lappa 3x, Phytolacca 3x,Symphytum 3x.

PURPOSE SECTION

Formulated for symptoms associated with arthritis, uric acid build-up, fibromyalgia, gout, rheumatism and other inflammatory conditions.

INACTIVE INGREDIENT SECTION

Inactive Ingredients: USP Purified Water; USP Gluten-free, non-GMO, organic cane dispensing alcohol 20%.

QUESTIONS? SECTION

www.newtonlabs.net Newton Laboratories, Inc. FDA Est # 1051203 -Conyers, GA 30012
Questions? 1.800.448.7256

WARNINGS SECTION

Warning: Do not use if tamper - evident seal is broken or missing. Consult a licensed healthcare professional if pregnant, nursing or if symptoms worsen or persist for more than a few days. Keep out of reach of children.

PREGNANCY OR BREAST FEEDING SECTION

Consult a licensed healthcare professional if pregnant, nursing or if symptoms worsen or persist for more than a few days

KEEP OUT OF REACH OF CHILDREN SECTION

Keep out of reach of children.